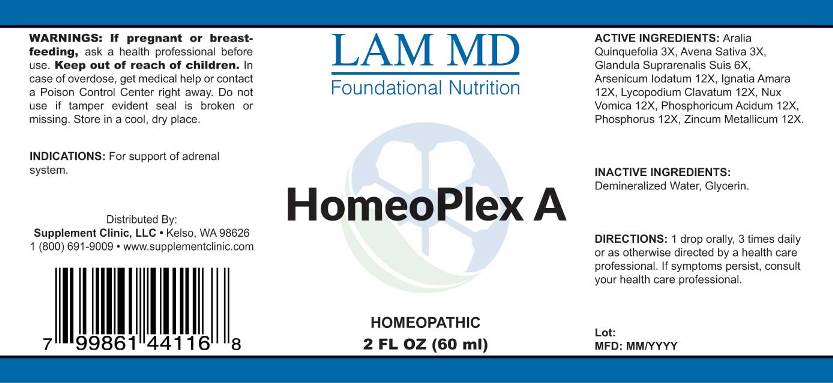 DRUG LABEL: Homeoplex A
NDC: 71781-0001 | Form: LIQUID
Manufacturer: Supplement Clinic, LLC.
Category: homeopathic | Type: HUMAN OTC DRUG LABEL
Date: 20171101

ACTIVE INGREDIENTS: AMERICAN GINSENG 3 [hp_X]/1 mL; AVENA SATIVA FLOWERING TOP 3 [hp_X]/1 mL; SUS SCROFA ADRENAL GLAND 6 [hp_X]/1 mL; ARSENIC TRIIODIDE 12 [hp_X]/1 mL; STRYCHNOS IGNATII SEED 12 [hp_X]/1 mL; LYCOPODIUM CLAVATUM SPORE 12 [hp_X]/1 mL; STRYCHNOS NUX-VOMICA SEED 12 [hp_X]/1 mL; PHOSPHORIC ACID 12 [hp_X]/1 mL; PHOSPHORUS 12 [hp_X]/1 mL; ZINC 12 [hp_X]/1 mL
INACTIVE INGREDIENTS: WATER; GLYCERIN

Drug Facts:

ACTIVE INGREDIENTS:

Aralia Quinquefolia 3X, Avena Sativa 3X, Glandula Suprarenalis Suis 6X, Arsenicum Iodatum 12X, Ignatia Amara, Lycopodium Clavatum 12X, Nux Vomica 12X, Phosphoricum Acidum 12X, Phosphorus 12X, Zincum Metallicum 12X.

INDICATIONS:

For support of adrenal system.

WARNINGS:

If pregnant or breast-feeding, ask a health professional before use.
Keep out of reach of children. In case of overdose, get medical help or contact a Poison Control Center right away.
Do not use if tamper evident seal is broken or missing.
Store in cool, dry place.

Keep out of reach of children. In case of overdose, get medical help or contact a Poison Control Center right away.

DIRECTIONS:

1 drop orally, 3 times daily or as otherwise directed by a health care professional. If symptoms persist, consult your health care professional.

INDICATIONS:

For support of adrenal system.

INACTIVE INGREDIENTS:

Demineralized Water, Glycerin

QUESTIONS:

Distributed By:

Supplement Clinic, LLC. •Kelso, WA 98626

1(800)691-9009 • www.supplementclinic.com

PACKAGE LABEL DISPLAY:

LAM MD

Foundational Nutrition

HomeoPlex A

HOMEOPATHIC

2 FL OZ (60 ml)